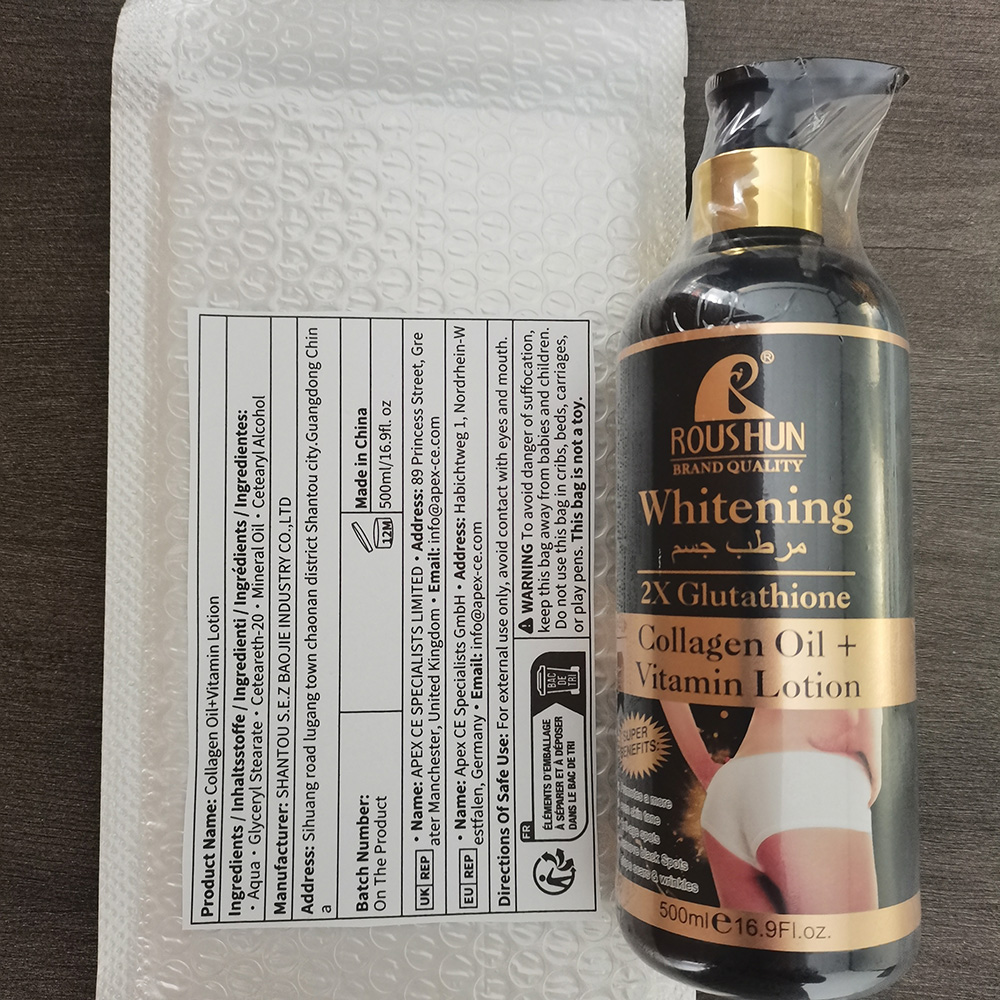 DRUG LABEL: Collagen Oil Vitamin
NDC: 84551-010 | Form: LOTION
Manufacturer: Kunshan Julian Trading Co., Ltd.
Category: otc | Type: HUMAN OTC DRUG LABEL
Date: 20240714

ACTIVE INGREDIENTS: CETEARETH-2 10 g/500 g; GLYCERYL STEARATE SE 25 g/500 g
INACTIVE INGREDIENTS: WATER 427.5 g/500 g; MINERAL OIL 20 g/500 g

ACTIVE INGREDIENT

WATER(AQUA) 85.5%

CETEARYL ALCOHOL 2%

MINERAL OIL 4%

CETEARETH-20 3.5%

GLYCERYL STEARATE 5%

purpose

whitening

Uses

Help to whiten
If used with other whitening products, it can remove dark spots and the risk of early skin aging

Warnings

For extemal use only

Stop use and ask a doctor if

rash occurs

Do not use

on damaged or broken skin

Keep out of reach of children

If swallowed,get medical help or contact a Poison Control Center right away.

When using this product

Keep out of eyes.Rinse with water to remove.

Ues

Help to whiten
If used with other whitening products, it can remove dark spots and the risk of early skin aging

Dosage and administration section

Dosage:Bid 30ml

Administration section:Systemic

Inactive ingredient section

Water